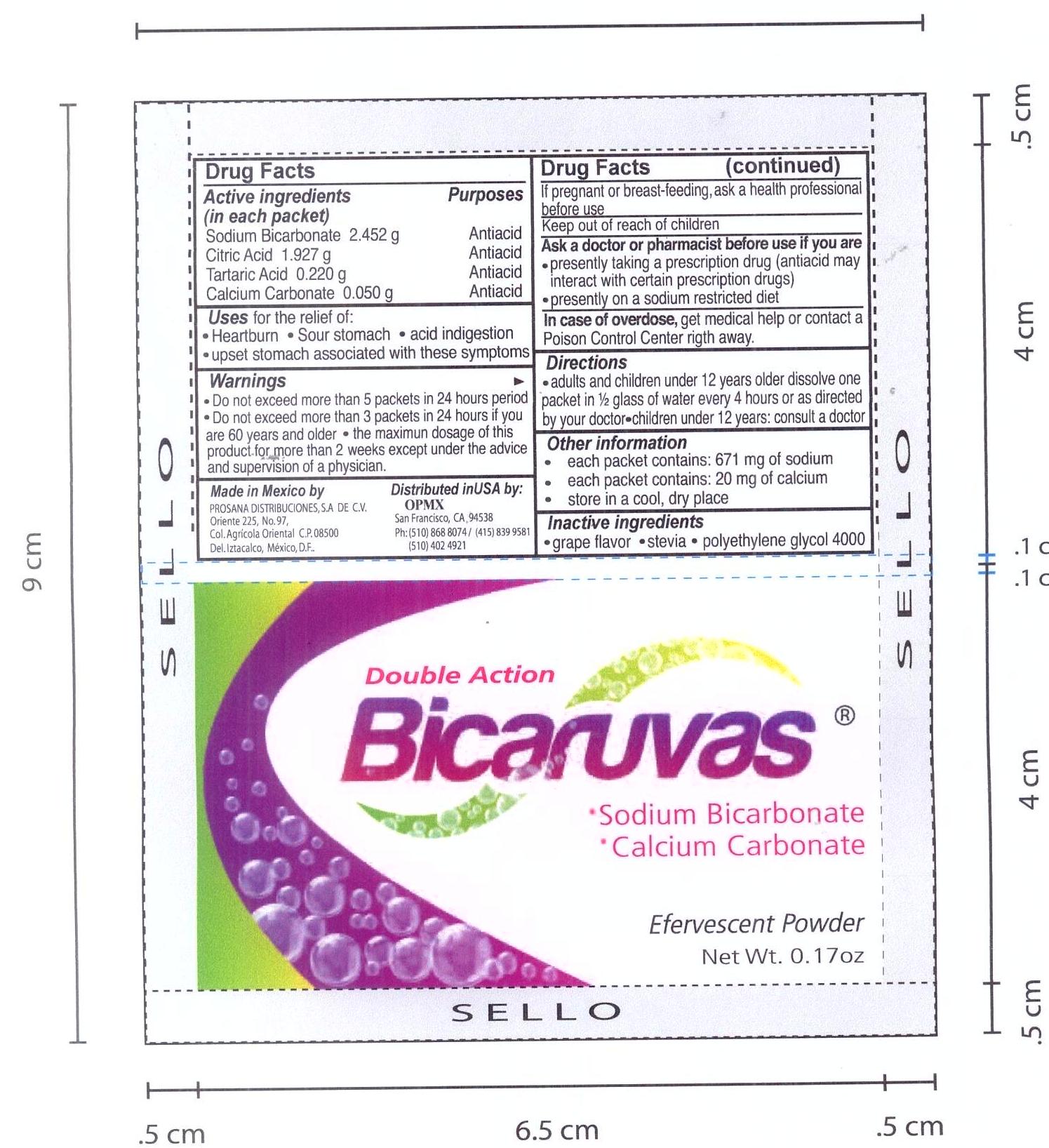 DRUG LABEL: BICARUVAS
NDC: 69728-0002 | Form: POWDER, FOR SOLUTION
Manufacturer: PROSANA DISTRIBUCIONES, S.A. DE C.V.
Category: otc | Type: HUMAN OTC DRUG LABEL
Date: 20150920

ACTIVE INGREDIENTS: TARTARIC ACID 220 mg/118 mL; CALCIUM CARBONATE 50 mg/118 mL; CITRIC ACID MONOHYDRATE 1827 mg/118 mL; SODIUM BICARBONATE 2452 mg/118 mL
INACTIVE INGREDIENTS: GRAPE 150 mg/118 mL; STEVIA LEAF 50 mg/118 mL; POLYETHYLENE GLYCOL 4000 150 mg/118 mL

Bicaruvas Double Action Antacid

Bicaruvas

Double Action

BICARUVAS

.Sodium Bicarbonate

.Calcium Carbonate

Antiacid

Effervescent Powder

8 packets .17 oz (5g) ea.

Directions

.Adult and children 12 years older dissolve one packet in 1/2 glass of water every 4 hours or as directed by your doctor.

Children under 12 years, consult a doctor

Active ingredients

Active Ingredients (in each packet) Purpose

Sodium Bicarbonate 2.452g antacid

Citric Acid 1.927 g antiacid

Tartaric Acid 0.220g antiacid

Calcium Carbonate .05 g antiacid

Uses

Uses for the relief of:

Heartburn . Sour stomach . upset stomach associated with these symptoms

Warnings

Warnings Do not exceed more than 5 packets in a 24 hour period

Do not exceed more than 3 packets in 24 hours if you are 60 years or older

the maximum dosage for more than two weeks except under the advise and supervision of a physician

Pregnant

If pregnant or breat feeding, ask a helth professional before use

Overdose

In case of Overdose get medical help or contact a Poison Control Center right away.

Inactive

Inactive Ingredients

grape flavor. stevia. polyethilene glycol 4000

Other Information

each packet contains 671 mg of sodium

each packet contains 20 mg of calcium

store in a dry cool place

children

Keep out of reach of children